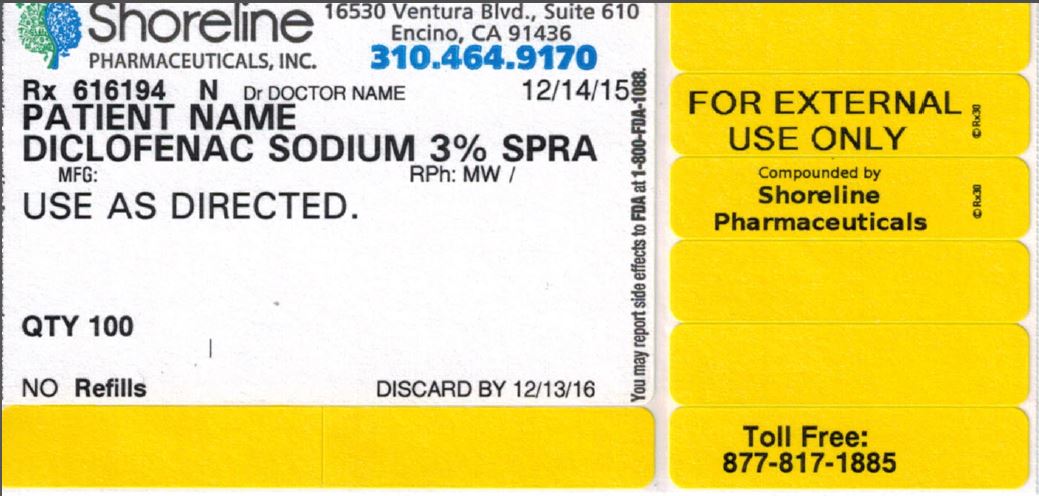 DRUG LABEL: Diclofenac Sodium
NDC: 69621-300 | Form: AEROSOL, METERED
Manufacturer: Shoreline Pharmaceuticals, Inc.
Category: prescription | Type: HUMAN PRESCRIPTION DRUG LABEL
Date: 20160310

ACTIVE INGREDIENTS: DICLOFENAC SODIUM 30 mg/1 mL

3% Diclofenac Spray, 118ml

GENERAL PRECAUTIONS

Diclofenac sodium 3% spray

Use as directed.

Qty 118

No refills

Shoreline Pharmaceuticals, Inc.

16530 Ventura Blvd, Suite 610

Encino, CA 91436

310.464.9170

Rx 616194

N Dr:

Date

Discard by

For External Use Only

Compounded by Shoreline Pharmaceuticals

Toll Free: 877-817-1885

You may report side effects to FDA at 1-800-FDA-1088